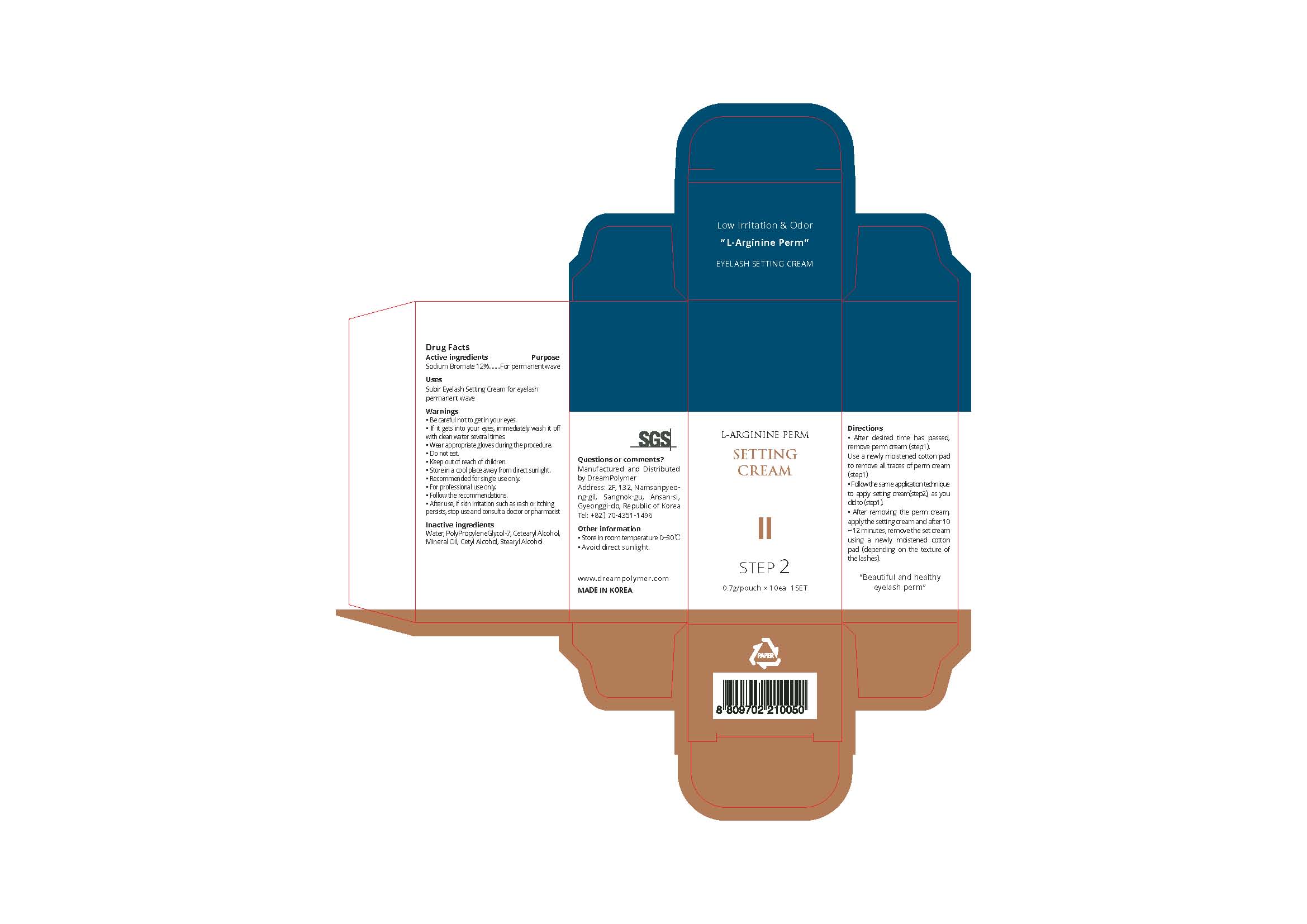 DRUG LABEL: SUBIR EYELASH
NDC: 81716-003 | Form: CREAM
Manufacturer: Dream Polymer
Category: otc | Type: HUMAN OTC DRUG LABEL
Date: 20210331

ACTIVE INGREDIENTS: STRONTIUM BROMATE 0.084 g/0.7 g
INACTIVE INGREDIENTS: Water; Cetyl Alcohol; Stearyl Alcohol

Active Ingredient(s)

Sodium Bromate 12%

Purpose

For permanent wave

Use

Subir Eyelash Setting Cream for eyelash permanent wave

Warnings

• Be careful not to get in your eyes.
• If it gets into your eyes, immediately wash it off with clean water several times.
• Wear appropriate gloves during the procedure.
• Do not eat.
• Keep out of reach of children.
• Store in a cool place away from direct sunlight.
• Recommended for single use only.
• For professional use only.
• Follow the recommendations.
• After use, if skin irritation such as rash or itching persists, stop use and consult a doctor or pharmacist

 Keep out of reach of children.

Directions

• After desired time has passed, remove perm cream (step1). Use a newly moistened cotton pad to remove all traces of perm cream (step1)
• Follow the same application technique to apply setting cream(step2), as you did to (step1).
• After removing the perm cream, apply the setting cream and after 10 ~ 12 minutes, remove the set cream using a newly moistened cotton pad (depending on the texture of the lashes).

Other information

・ Store in room temperature 0~30℃
・ Avoid direct sunlight.

Inactive ingredients

Water, PolyPropyleneGlycol-7, Cetearyl Alcohol, Mineral Oil, Cetyl Alcohol, Stearyl Alcohol